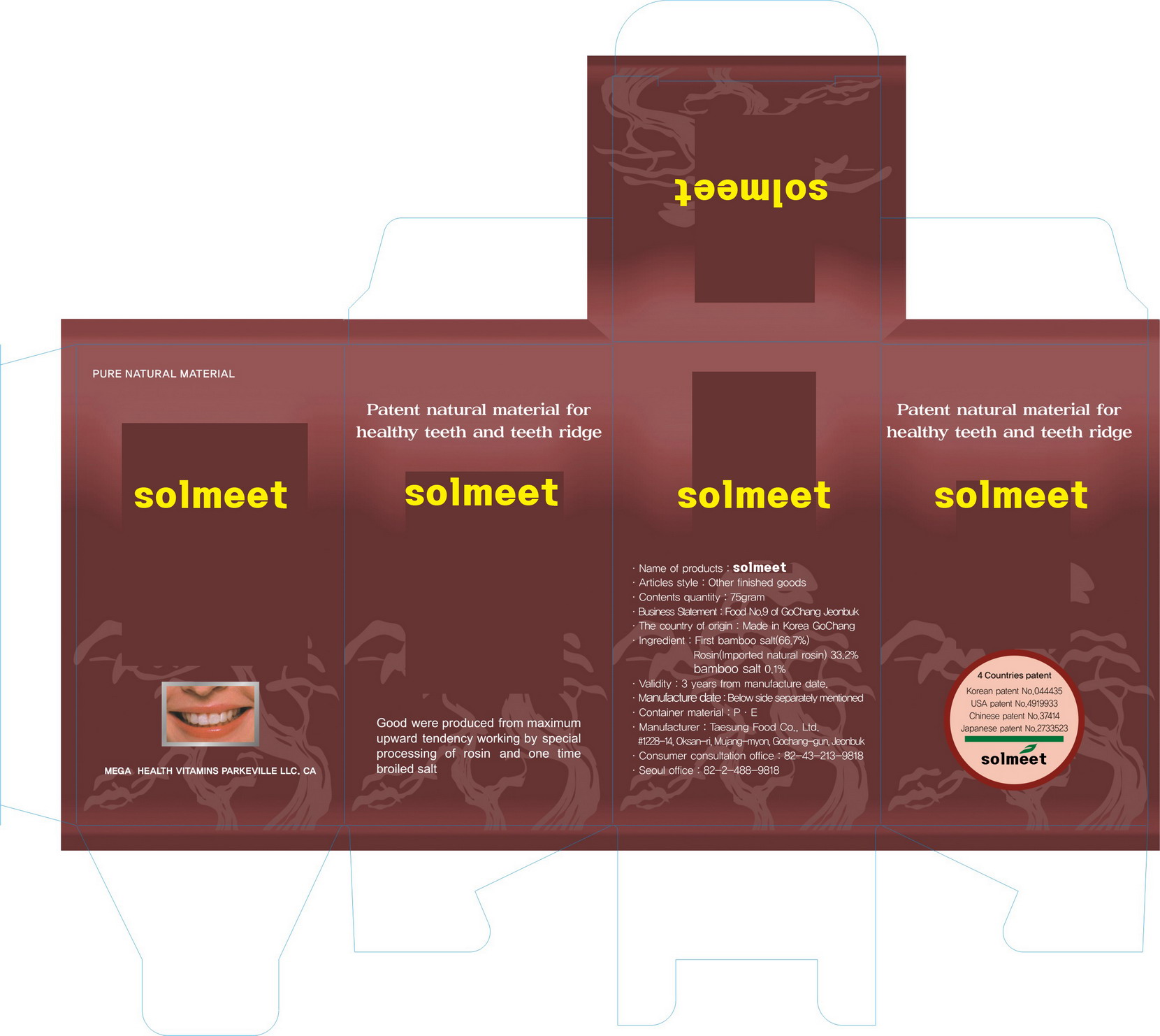 DRUG LABEL: Solmeet
NDC: 70706-1002 | Form: POWDER, DENTIFRICE
Manufacturer: SOLM Co., Ltd.
Category: otc | Type: HUMAN OTC DRUG LABEL
Date: 20191222

ACTIVE INGREDIENTS: ROSIN 0.332 1/100 g
INACTIVE INGREDIENTS: SODIUM CHLORIDE

ACTIVE INGREDIENT

Rosin

INACTIVE INGREDIENT

Sodium chloride

PURPOSE

for dental care

keep out of reach of the children

INDICATIONS AND USAGE

use when is needed

WARNINGS

- do not swallow when using this product

- if more than used for rinsing is accidentally swallowed, get medical helps or contact a poison control center right away

DOSAGE AND ADMINISTRATION

Hold 1 grams in mouth for 1~2 minutes then rinse out with water